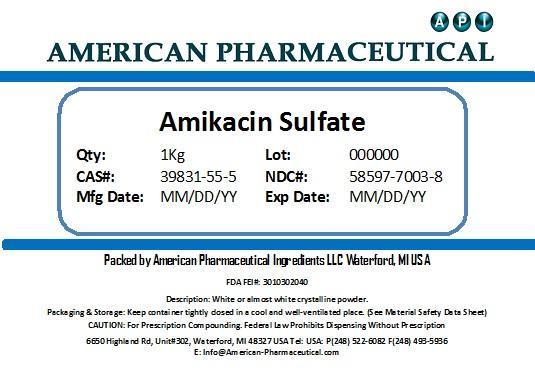 DRUG LABEL: Amikacin Sulfate
NDC: 58597-7003 | Form: POWDER
Manufacturer: AMERICAN PHARMACEUTICAL INGREDIENTS LLC
Category: other | Type: BULK INGREDIENT
Date: 20131031

ACTIVE INGREDIENTS: AMIKACIN SULFATE 1 g/1 g

Amikacin Sulfate